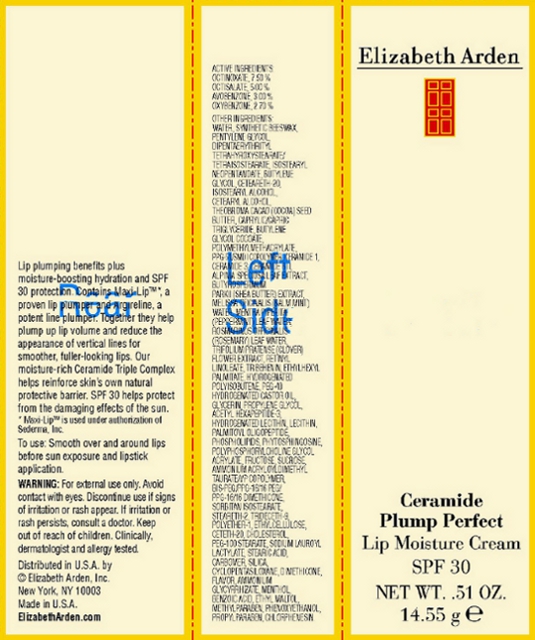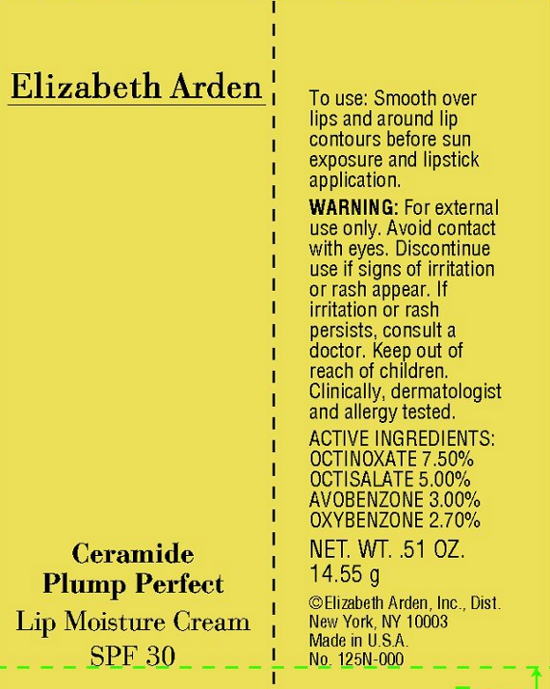 DRUG LABEL: Ceramide Plump Perfect Lip Moisture SPF 30
NDC: 67938-0967 | Form: CREAM
Manufacturer: Elizabeth Arden, Inc
Category: otc | Type: HUMAN OTC DRUG LABEL
Date: 20110718

ACTIVE INGREDIENTS: OCTINOXATE 1.091 g/14.55 g; OCTISALATE 0.7275 g/14.55 g; AVOBENZONE 0.4365 g/14.55 g; OXYBENZONE 0.3928 g/14.55 g
INACTIVE INGREDIENTS: WATER; PENTYLENE GLYCOL; BUTYLENE GLYCOL; POLYOXYL 20 CETOSTEARYL ETHER; ISOSTEARYL ALCOHOL; CETOSTEARYL ALCOHOL; COCOA BUTTER; MEDIUM-CHAIN TRIGLYCERIDES; PEG-100 STEARATE; PHENOXYETHANOL; ETHYLHEXYL PALMITATE; DIMETHICONE; SILICON DIOXIDE; STEARETH-2; CETETH-20; TRIBEHENIN; GLYCYRRHIZIN, AMMONIATED; POLYOXYL 40 HYDROGENATED CASTOR OIL; STEARIC ACID; CHLORPHENESIN; CYCLOMETHICONE 5; ETHYLCELLULOSES; MENTHOL; TRIFOLIUM PRATENSE FLOWER; SUCROSE; FRUCTOSE; METHYLPARABEN; GLYCERIN; BENZOIC ACID; PROPYLENE GLYCOL; SODIUM LAUROYL LACTYLATE; ETHYL MALTOL; PEPPERMINT OIL; ROSEMARY OIL; CERAMIDE 3; PALMITOYL OLIGOPEPTIDE; XANTHAN GUM; ACETYL HEXAPEPTIDE-3; PROPYLPARABEN; ALPINIA ZERUMBET LEAF; BUTYLPARABEN; ETHYLPARABEN; CHOLESTEROL; ISOBUTYLPARABEN

BC0967

DESCRIPTION

Lip plumping benefits plus moisture-boosting hydration and SPF 30 protection. Contains Maxi-Lip, a proven lip plump plump, and Argireline, a potent lip plumper. Together they help plump up lip volume and reduce the appearance of vertical lines for smoother, fuller-looking lips. Our moisture-rich Ceramide Triple Complex helps reinforce skin's own natural protective barrier. SPF 30 helps protect from the damaging effects of the sun.

INDICATIONS AND USAGE

To Use: Smooth over and around lips before sun exposure and lipstick application.

WARNINGS

WARNING: For external use only. Avoid contact with eyes. Discontinue use if signs of irritation or rash appear. If irritation or rash persists, consult a doctor. Keep out of reach of children. Clinically, dermatologist, and allergy tested.

OTC - ACTIVE INGREDIENT

Active Ingredients: Octinoxate 7.50 %, Octisalate 5.00%, Avobenzone 3.00%, Oxybenzone 2.70%.

INACTIVE INGREDIENT

Other Ingredients: Water, Synthetic Beeswax, Pentylene Glycol, Dipentaerythrityl Tetrahyroxystearate/Tetreisostearate, Isostearyl Neopentanoate, Butylene Gloycol, Ceteareth-20, Isostearyl Alcohol, Cetearyl Alcohol, Theobroma Cacao (Cocoa) Seed Butter, Caprylic/Capric Triglyceride, Butylene Glycol Cocoate, Polymethylmethacrylate, PPG-51/SMDI Coplymer, Ceramide 1, Ceramide 3, Ceramide 6 II, Alpinia Speciosa Leaf Extract, Butrospermum Park II (Shea Butter) Extract, Melissa Oficinalis (Balm Mint) Water, Mentha Piperita (Peppermint) Leaf Water, Rosmarinus Officinalis (Rosemary) Leaf Water, Trifolium Pratense (Clover) Flower Extract, Retinyl Linoleate, Tribehenin, Ethylhexyl Palmitate, Hydrogenated Polysobutene, PEG-40 Hydrogenated Castor Oil, Glycerin, Propylene Glycol, Acetyl Hexapeptide-3, Hydrogenated Lecithin, Lecithin, Palmitoyl Oligopeptide, Phospholipids, Phytospingosine, Polyphosphorylcholine Glycol, Acrylate, Fructose, Sucrose, Ammonium Acryloyldimethyl Taurate/VP Copolymer, BIS-PEG/PPG-16/16PEG/PPG-16/16 Dimethicone, Sorbitan Isostearate, Steareth-2, Tridecth-9, Polyether-1, Ethylcellulose, Ceteth-20, Colesterol, PEG-100 Stearate, Sodium Lauroyl Lactylate, Stearic Acid, Carbomer, Silica, Cyclopentasiloxane, Dimethicone, Flavor, Ammonium Cylcyrrhizate, Menthol, Benzoic Acid, Ethyl Maltol, Methylparaben, Phenoxyethanol, Propylparaben, Chlophenesin.

DOSAGE & ADMINISTRATION

Smooth over and around lips.

OTC - KEEP OUT OF REACH OF CHILDREN

Keep out of reach of children.

OTC - PURPOSE

Provides SPF 30 sun protection.

OTC - WHEN USING

Avoid contact with eyes.